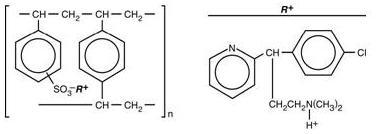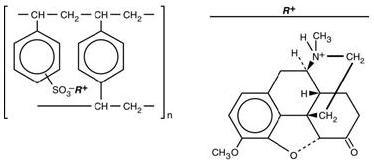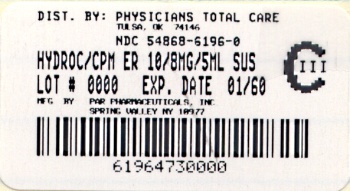 DRUG LABEL: Hydrocodone Polistirex and Chlorpheniramine Polistirex
NDC: 54868-6196 | Form: SUSPENSION
Manufacturer: Physicians Total Care, Inc.
Category: prescription | Type: HUMAN PRESCRIPTION DRUG LABEL
Date: 20101014
DEA Schedule: CIII

ACTIVE INGREDIENTS: HYDROCODONE BITARTRATE 10 mg/5 mL; CHLORPHENIRAMINE MALEATE 8 mg/5 mL
INACTIVE INGREDIENTS: ASCORBIC ACID; D&C YELLOW NO. 10; HIGH FRUCTOSE CORN SYRUP; METHYLPARABEN; POLYSORBATE 80; PROPYLENE GLYCOL; PROPYLPARABEN; WATER; SODIUM ASCORBATE; SODIUM METABISULFITE; SODIUM POLYSTYRENE SULFONATE; SUCROSE; TRIACETIN; XANTHAN GUM

Hydrocodone Polistirex and Chlorpheniramine Polistirex Extended Release Oral Suspension
10 mg hydrocodone bitartrate and 8 mg chlorpheniramine maleate per 5 mL
(CIII)
Rx only

DESCRIPTION

Each teaspoonful (5 mL) of hydrocodone polistirex and chlorpheniramine polistirex extended release (ER) oral suspension contains hydrocodone polistirex equivalent to 10 mg of hydrocodone bitartrate and chlorpheniramine polistirex equivalent to 8 mg of chlorpheniramine maleate. Hydrocodone polistirex and chlorpheniramine polistirex ER oral suspension provides up to 12-hour relief per dose. Hydrocodone is a centrally-acting narcotic antitussive. Chlorpheniramine is an antihistamine. Hydrocodone polistirex and chlorpheniramine polistirex ER oral suspension is for oral use only.

Hydrocodone Polistirex

Sulfonated styrene-divinylbenzene copolymer complex with 4,5α-epoxy-3-methoxy-17-methylmorphinan-6-one.

Chlorpheniramine Polistirex

Sulfonated styrene-divinylbenzene copolymer complex with 2-[p-chloro-α-[2-(dimethylamino)ethyl]-benzyl]pyridine.

Inactive Ingredients

Ascorbic acid, D&C Yellow No. 10, flavors, high fructose corn syrup, modified food starch, methylparaben, polysorbate 80, polyvinyl acetate, propylene glycol, propylparaben, purified water, sodium ascorbate, sodium metabisulfite, sodium polystyrene sulfonate, sucrose, triacetin, xanthan gum.

CLINICAL PHARMACOLOGY

Hydrocodone is a semisynthetic narcotic antitussive and analgesic with multiple actions qualitatively similar to those of codeine. The precise mechanism of action of hydrocodone and other opiates is not known; however, hydrocodone is believed to act directly on the cough center. In excessive doses, hydrocodone, like other opium derivatives, will depress respiration. The effects of hydrocodone in therapeutic doses on the cardiovascular system are insignificant. Hydrocodone can produce miosis, euphoria, and physical and psychological dependence.

Chlorpheniramine is an antihistamine drug (H1 receptor antagonist) that also possesses anticholinergic and sedative activity. It prevents released histamine from dilating capillaries and causing edema of the respiratory mucosa.

Hydrocodone release from hydrocodone polistirex and chlorpheniramine polistirex ER oral suspension is controlled by an extended-release drug delivery system, which combines an ion-exchange polymer matrix with a diffusion rate-limiting permeable coating. Chlorpheniramine release is prolonged by use of an ion-exchange polymer system.

Following multiple dosing with hydrocodone polistirex and chlorpheniramine polistirex ER oral suspension, hydrocodone mean (S.D.) peak plasma concentrations of 22.8 (5.9) ng/mL occurred at 3.4 hours. Chlorpheniramine mean (S.D.) peak plasma concentrations of 58.4 (14.7) ng/mL occurred at 6.3 hours following multiple dosing. Peak plasma levels obtained with an immediate-release syrup occurred at approximately 1.5 hours for hydrocodone and 2.8 hours for chlorpheniramine. The plasma half-lives of hydrocodone and chlorpheniramine have been reported to be approximately 4 and 16 hours, respectively.

INDICATIONS AND USAGE

Hydrocodone polistirex and chlorpheniramine polistirex ER oral suspension is indicated for relief of cough and upper respiratory symptoms associated with allergy or a cold in adults and children 6 years of age and older.

CONTRAINDICATIONS

Hydrocodone polistirex and chlorpheniramine polistirex ER oral suspension is contraindicated in patients with a known allergy or sensitivity to hydrocodone or chlorpheniramine.

The use of hydrocodone polistirex and chlorpheniramine polistirex ER oral suspension is contraindicated in children less than 6 years of age due to the risk of fatal respiratory depression.

WARNINGS

Contains sodium metabisulfite, a sulfite that may cause allergic-type reactions including anaphylactic symptoms and life-threatening or less severe asthmatic episodes in certain susceptible people. The overall prevalence of sulfite sensitivity in the general population is unknown and probably low. Sulfite sensitivity is seen more frequently in asthmatic than in nonasthmatic people.

Respiratory Depression

As with all narcotics, hydrocodone polistirex and chlorpheniramine polistirex ER oral suspension produces dose-related respiratory depression by directly acting on brain stem respiratory centers. Hydrocodone affects the center that controls respiratory rhythm and may produce irregular and periodic breathing. Caution should be exercised when hydrocodone polistirex and chlorpheniramine polistirex ER oral suspension is used postoperatively and in patients with pulmonary disease, or whenever ventilatory function is depressed. If respiratory depression occurs, it may be antagonized by the use of naloxone hydrochloride and other supportive measures when indicated (see OVERDOSAGE).

Head Injury and Increased Intracranial Pressure

The respiratory depressant effects of narcotics and their capacity to elevate cerebrospinal fluid pressure may be markedly exaggerated in the presence of head injury, other intracranial lesions, or a pre-existing increase in intracranial pressure. Furthermore, narcotics produce adverse reactions, which may obscure the clinical course of patients with head injuries.

Acute Abdominal Conditions

The administration of narcotics may obscure the diagnosis or clinical course of patients with acute abdominal conditions.

Obstructive Bowel Disease

Chronic use of narcotics may result in obstructive bowel disease especially in patients with underlying intestinal motility disorder.

Pediatric Use

The use of hydrocodone polistirex and chlorpheniramine polistirex ER oral suspension is contraindicated in children less than 6 years of age (see CONTRAINDICATIONS).

In pediatric patients, as well as adults, the respiratory center is sensitive to the depressant action of narcotic cough suppressants in a dose-dependent manner. Caution should be exercised when administering hydrocodone polistirex and chlorpheniramine polistirex ER oral suspension to pediatric patients 6 years of age and older. Overdose or concomitant administration of hydrocodone polistirex and chlorpheniramine polistirex ER oral suspension with other respiratory depressants may increase the risk of respiratory depression in pediatric patients. Benefit to risk ratio should be carefully considered, especially in pediatric patients with respiratory embarrassment (e.g., croup) (see PRECAUTIONS).

PRECAUTIONS

General

Caution is advised when prescribing this drug to patients with narrow-angle glaucoma, asthma, or prostatic hypertrophy.

Special Risk Patients

As with any narcotic agent, hydrocodone polistirex and chlorpheniramine polistirex ER oral suspension should be used with caution in elderly or debilitated patients and those with severe impairment of hepatic or renal function, hypothyroidism, Addison's disease, prostatic hypertrophy, or urethral stricture. The usual precautions should be observed and the possibility of respiratory depression should be kept in mind.

Information for Patients

As with all narcotics, hydrocodone polistirex and chlorpheniramine polistirex ER oral suspension may produce marked drowsiness and impair the mental and/or physical abilities required for the performance of potentially hazardous tasks such as driving a car or operating machinery; patients should be cautioned accordingly. Hydrocodone polistirex and chlorpheniramine polistirex ER oral suspension must not be diluted with fluids or mixed with other drugs as this may alter the resin-binding and change the absorption rate, possibly increasing the toxicity.

Patients should be advised to measure hydrocodone polistirex and chlorpheniramine polistirex ER oral suspension with an accurate measuring device. A household teaspoon is not an accurate measuring device and could lead to overdosage, especially when a half a teaspoon is measured. A pharmacist can recommend an appropriate measuring device and can provide instructions for measuring the correct dose.

Shake well before using.

Keep out of the reach of children.

Cough Reflex

Hydrocodone suppresses the cough reflex; as with all narcotics, caution should be exercised when hydrocodone polistirex and chlorpheniramine polistirex ER oral suspension is used postoperatively, and in patients with pulmonary disease.

Drug Interactions

Patients receiving narcotics, antihistaminics, antipsychotics, antianxiety agents, or other CNS depressants (including alcohol) concomitantly with hydrocodone polistirex and chlorpheniramine polistirex ER oral suspension may exhibit an additive CNS depression. When combined therapy is contemplated, the dose of one or both agents should be reduced.

The use of MAO inhibitors or tricyclic antidepressants with hydrocodone preparations may increase the effect of either the antidepressant or hydrocodone.

The concurrent use of other anticholinergics with hydrocodone may produce paralytic ileus.

Carcinogenesis and Mutagenesis and Impairment of Fertility

Carcinogenicity, mutagenicity, and reproductive studies have not been conducted with hydrocodone polistirex and chlorpheniramine polistirex ER oral suspension.

Pregnancy

Teratogenic Effects - Pregnancy Category C

Hydrocodone has been shown to be teratogenic in hamsters when given in doses 700 times the human dose. There are no adequate and well-controlled studies in pregnant women. Hydrocodone polistirex and chlorpheniramine polistirex ER oral suspension should be used during pregnancy only if the potential benefit justifies the potential risk to the fetus.

Nonteratogenic Effects

Babies born to mothers who have been taking opioids regularly prior to delivery will be physically dependent. The withdrawal signs include irritability and excessive crying, tremors, hyperactive reflexes, increased respiratory rate, increased stools, sneezing, yawning, vomiting, and fever. The intensity of the syndrome does not always correlate with the duration of maternal opioid use or dose.

Labor and Delivery

As with all narcotics, administration of hydrocodone polistirex and chlorpheniramine polistirex ER oral suspension to the mother shortly before delivery may result in some degree of respiratory depression in the newborn, especially if higher doses are used.

Nursing Mothers

It is not known whether this drug is excreted in human milk. Because many drugs are excreted in human milk and because of the potential for serious adverse reactions in nursing infants from hydrocodone polistirex and chlorpheniramine polistirex ER oral suspension, a decision should be made whether to discontinue nursing or to discontinue the drug, taking into account the importance of the drug to the mother.

Pediatric Use

The use of hydrocodone polistirex and chlorpheniramine polistirex ER oral suspension is contraindicated in children less than 6 years of age (see CONTRAINDICATIONS and ADVERSE REACTIONS, Respiratory, Thoracic and Mediastinal Disorders).

Hydrocodone polistirex and chlorpheniramine polistirex ER oral suspension should be used with caution in pediatric patients 6 years of age and older (see WARNINGS, Pediatric Use).

Geriatric Use

Clinical studies of hydrocodone polistirex and chlorpheniramine polistirex ER oral suspension did not include sufficient numbers of subjects aged 65 and over to determine whether they respond differently from younger subjects. Other reported clinical experience has not identified differences in responses between the elderly and younger patients. In general, dose selection for an elderly patient should be cautious, usually starting at the low end of the dosing range, reflecting the greater frequency of decreased hepatic, renal, or cardiac function, and of concomitant disease or other drug therapy.

This drug is known to be substantially excreted by the kidney, and the risk of toxic reactions to this drug may be greater in patients with impaired renal function. Because elderly patients are more likely to have decreased renal function, care should be taken in dose selection, and it may be useful to monitor renal function.

ADVERSE REACTIONS

Gastrointestinal Disorders

Nausea and vomiting may occur; they are more frequent in ambulatory than in recumbent patients. Prolonged administration of hydrocodone polistirex and chlorpheniramine polistirex ER oral suspension may produce constipation.

General Disorders and Administration Site Conditions

Death

Nervous System Disorders

Sedation, drowsiness, mental clouding, lethargy, impairment of mental and physical performance, anxiety, fear, dysphoria, euphoria, dizziness, psychic dependence, mood changes.

Renal and Urinary Disorders

Ureteral spasm, spasm of vesical sphincters, and urinary retention have been reported with opiates.

Respiratory, Thoracic and Mediastinal Disorders

Dryness of the pharynx, occasional tightness of the chest, and respiratory depression (see CONTRAINDICATIONS).

Hydrocodone polistirex and chlorpheniramine polistirex ER oral suspension may produce dose-related respiratory depression by acting directly on brain stem respiratory centers (see OVERDOSAGE). Use of hydrocodone polistirex and chlorpheniramine polistirex ER oral suspension in children less than 6 years of age has been associated with fatal respiratory depression. Overdose with hydrocodone polistirex and chlorpheniramine polistirex ER oral suspension in children 6 years of age and older, in adolescents, and in adults has been associated with fatal respiratory depression.

Skin and Subcutaneous Tissue Disorders

Rash, pruritus.

DRUG ABUSE AND DEPENDENCE

Hydrocodone polistirex and chlorpheniramine polistirex ER oral suspension is a Schedule III narcotic. Psychic dependence, physical dependence and tolerance may develop upon repeated administration of narcotics; therefore, hydrocodone polistirex and chlorpheniramine polistirex ER oral suspension should be prescribed and administered with caution. However, psychic dependence is unlikely to develop when hydrocodone polistirex and chlorpheniramine polistirex ER oral suspension is used for a short time for the treatment of cough. Physical dependence, the condition in which continued administration of the drug is required to prevent the appearance of a withdrawal syndrome, assumes clinically significant proportions only after several weeks of continued oral narcotic use, although some mild degree of physical dependence may develop after a few days of narcotic therapy.

OVERDOSAGE

Signs and Symptoms

Serious overdosage with hydrocodone is characterized by respiratory depression (a decrease in respiratory rate and/or tidal volume, Cheyne-Stokes respiration, cyanosis), extreme somnolence progressing to stupor or coma, skeletal muscle flaccidity, cold and clammy skin, and sometimes bradycardia and hypotension. Although miosis is characteristic of narcotic overdose, mydriasis may occur in terminal narcosis or severe hypoxia. In severe overdosage apnea, circulatory collapse, cardiac arrest and death may occur. The manifestations of chlorpheniramine overdosage may vary from central nervous system depression to stimulation.

Treatment

Primary attention should be given to the reestablishment of adequate respiratory exchange through provision of a patent airway and the institution of assisted or controlled ventilation. The narcotic antagonist naloxone hydrochloride is a specific antidote for respiratory depression which may result from overdosage or unusual sensitivity to narcotics including hydrocodone. Therefore, an appropriate dose of naloxone hydrochloride should be administered, preferably by the intravenous route, simultaneously with efforts at respiratory resuscitation. Since the duration of action of hydrocodone in this formulation may exceed that of the antagonist, the patient should be kept under continued surveillance and repeated doses of the antagonist should be administered as needed to maintain adequate respiration. For further information, see full prescribing information for naloxone hydrochloride. An antagonist should not be administered in the absence of clinically significant respiratory depression. Oxygen, intravenous fluids, vasopressors and other supportive measures should be employed as indicated. Gastric emptying may be useful in removing unabsorbed drug.

DOSAGE AND ADMINISTRATION

It is important that hydrocodone polistirex and chlorpheniramine polistirex ER oral suspension is measured with an accurate measuring device (see PRECAUTIONS, Information for Patients). A household teaspoon is not an accurate measuring device and could lead to overdosage, especially when half a teaspoon is to be measured. It is strongly recommended that an accurate measuring device be used. A pharmacist can provide an appropriate measuring device and can provide instructions for measuring the correct dose.

Shake well before using.

Adults and Children 12 Years and Older

5 mL (1 teaspoonful) every 12 hours; do not exceed 10 mL (2 teaspoonfuls) in 24 hours.

Children 6 to 11 Years of Age

2.5 mL (½ teaspoonful) every 12 hours; do not exceed 5 mL (1 teaspoonful) in 24 hours.

This medicine is contraindicated in children under 6 years of age (see CONTRAINDICATIONS).

HOW SUPPLIED

Hydrocodone polistirex and chlorpheniramine polistirex ER oral suspension, equivalent to 10 mg of hydrocodone bitartrate and 8 mg of chlorpheniramine maleate per 5 mL is a yellow viscous suspension.

NDC 54868-6196-0 473 mL bottle

Storage:

Shake well. Dispense in a well-closed container.

Store at 20 to 25°C (68 to 77°F); excursions permitted from 15 to 30°C (59 to 86°F)

[see USP Controlled Room Temperature].

Distributed by:

Par Pharmaceutical Companies, Inc.

Spring, Valley, NY 10977

LB8072

Rev 00 OS235-01-72-01

I 04/10

Relabeling of "Additional Barcode Label" by:
Physicians Total Care, Inc.
Tulsa, OK 74146